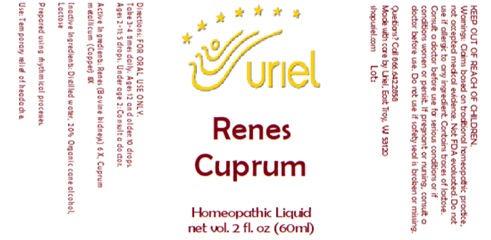 DRUG LABEL: Renes Cuprum
NDC: 48951-8405 | Form: LIQUID
Manufacturer: Uriel Pharmacy Inc.
Category: homeopathic | Type: HUMAN OTC DRUG LABEL
Date: 20250801

ACTIVE INGREDIENTS: PORK KIDNEY 6 [hp_X]/1 mL; COPPER 8 [hp_X]/1 mL
INACTIVE INGREDIENTS: WATER; LACTOSE; ALCOHOL

Renes Cuprum

INDICATIONS AND USAGE

Directions: FOR ORAL USE ONLY.

DOSAGE AND ADMINISTRATION

Take 3-4 times daily. Ages 12 and older: 10 drops. Ages 2-11: 5 drops. Under age 2: Consult a doctor.

ACTIVE INGREDIENT

Active Ingredients: Renes (Bovine kidneys) 6X, Cuprum metallicum (Copper) 8X

Inactive Ingredients: Distilled water, Lactose

"prepared using rhythmical processes"

PURPOSE

Use: Temporary relief of headache.

KEEP OUT OF REACH OF CHILDREN.

WARNINGS

Warnings: Claims based on traditional homeopathic practice, not accepted medical evidence. Not FDA evaluated. Do not use if allergic to any ingredient. Contains traces of lactose. Consult a doctor before use for serious conditions or if conditions worsen or persist. If pregnant or nursing, consult a doctor before use. Do not use if safety seal is broken or missing.

REFRIGERATE AFTER OPENING.
BEST WHEN USED WITHIN 90 DAYS OF OPENING.

QUESTIONS

Questions? Call 866.642.2858 Made with care by Uriel, East Troy, WI 53120 shopuriel.com